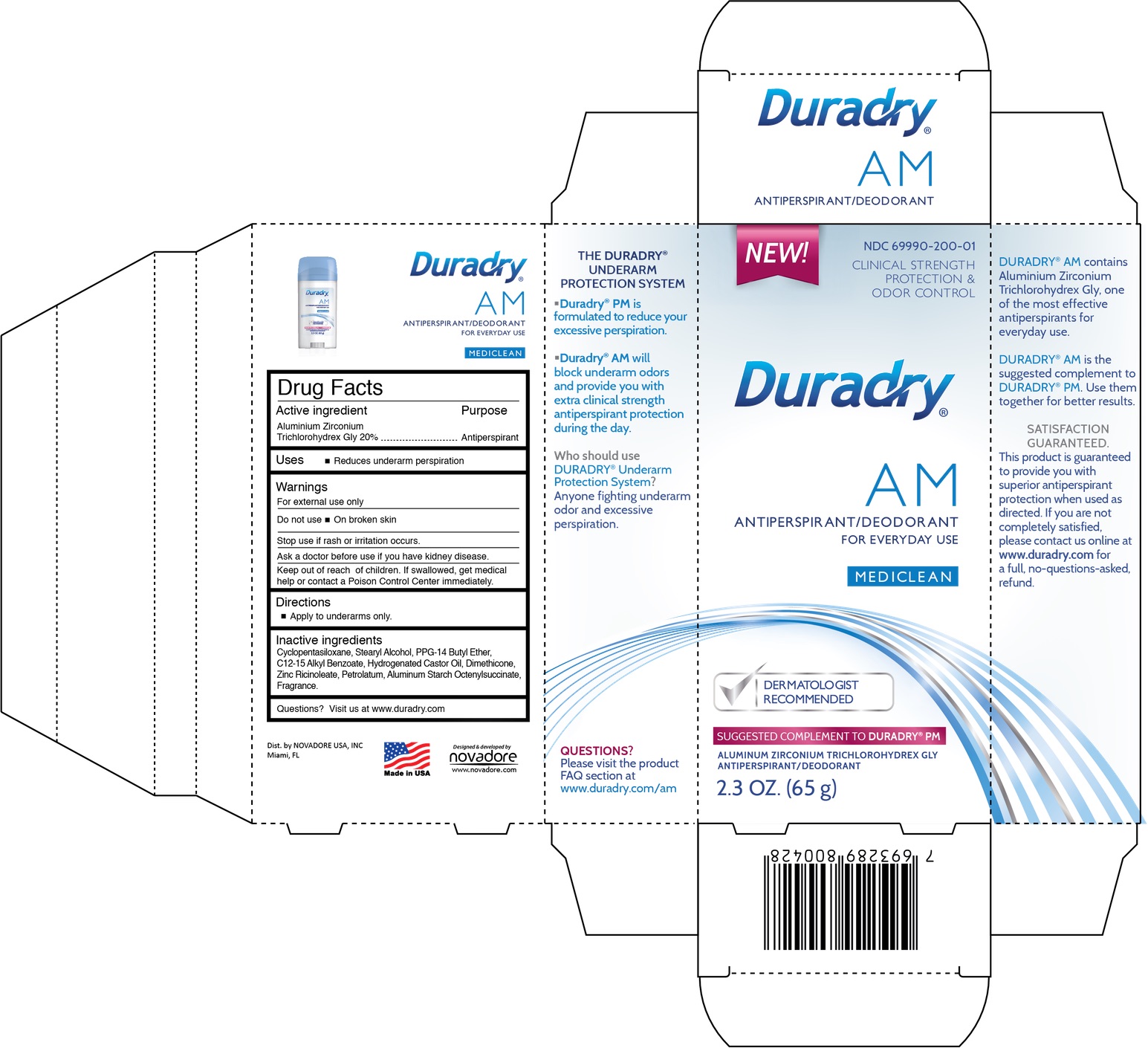 DRUG LABEL: DURADRY AM
NDC: 69990-200 | Form: STICK
Manufacturer: Novadore USA, LLC
Category: otc | Type: HUMAN OTC DRUG LABEL
Date: 20210607

ACTIVE INGREDIENTS: ALUMINUM ZIRCONIUM TRICHLOROHYDREX GLY 20 g/100 g
INACTIVE INGREDIENTS: CYCLOMETHICONE 5; STEARYL ALCOHOL; PPG-14 BUTYL ETHER; ALKYL (C12-15) BENZOATE; HYDROGENATED CASTOR OIL; DIMETHICONE; ZINC RICINOLEATE; PETROLATUM; ALUMINUM STARCH OCTENYLSUCCINATE

DURADRY AM Antiperspirant/Deodorant for everyday use

Active ingredient

Aluminum Zirconium Trichlorohydrex Glycine 20%

Purpose

Antiperspirant

Uses

Reduces underarm perspiration

Warnings

For external use only
Stop use if rash or irritation occurs.

Do not use

- On broken skin.

Ask a doctor before use

if you have kidney disease

Keep out of reach of children

If swallowed, get medical help or contact a Poison Control Center right away.

Directions

- Apply to underarms only.

Inactive ingredients

Cyclopentasiloxane, Stearyl Alcohol, PPG-14 Butyl Ether, C12-15 Alkyl Benzoate, Hydrogenated Castor Oil, Dimethicone, Zinc Ricinoleate, Petrolatum, Aluminum Starch Octenylsuccinate Fragrance.

Questions?

Visit us at www.duradry.com/am

Designed & developed by:
NOVADORE USA, INC
Miami, FL